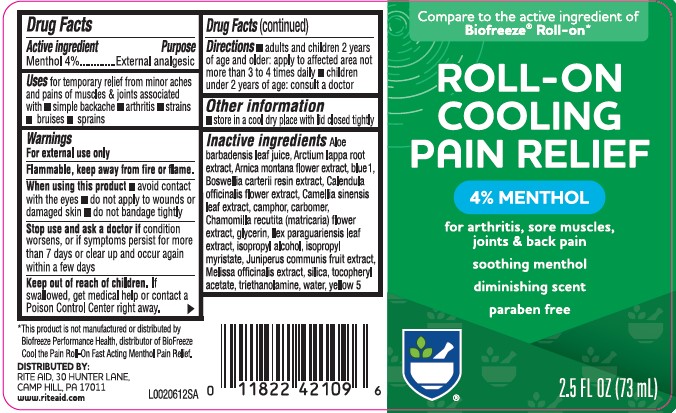 DRUG LABEL: Pain Relieving Gel
NDC: 11822-8940 | Form: GEL
Manufacturer: Rite Aid Corporation
Category: otc | Type: HUMAN OTC DRUG LABEL
Date: 20260130

ACTIVE INGREDIENTS: MENTHOL, UNSPECIFIED FORM 40 mg/1 mL
INACTIVE INGREDIENTS: CARBOMER HOMOPOLYMER, UNSPECIFIED TYPE; ILEX PARAGUARIENSIS LEAF; FRANKINCENSE; CHAMOMILE; CALENDULA OFFICINALIS FLOWER; ALOE VERA LEAF; ARCTIUM LAPPA ROOT; ARNICA MONTANA FLOWER; FD&C BLUE NO. 1; GREEN TEA LEAF; CAMPHOR (NATURAL); ISOPROPYL ALCOHOL; JUNIPER BERRY; MELISSA OFFICINALIS; SILICON DIOXIDE; TROLAMINE; FD&C YELLOW NO. 5; GLYCERIN; ISOPROPYL MYRISTATE; .ALPHA.-TOCOPHEROL ACETATE; WATER

Rite Aid 894.001/894AA rev 1
Cooling Pain Relief Gel

Active ingredient

Menthol 4%

Purpose

External analgesic

Uses

for temporary relief from minor aches and pains of muscles & joints associated with

- simple backache
- arthritis
- strains
- bruises
- sprains

Warnings

For external use only

Flammable, keep away from fire or flame.

When using this product

- avoid contact with the eyes
- do not apply to wounds or damaged skin
- do not bandage tightly

Stop use and ask a doctor if

condition worsens, or if symptoms persist for more than 7 days or clear up and occur again within a few days

Keep out of reach of children.

If swallowed, get medical help or contact a Poison Control Center right away.

Directions

- adults and children 2 years of age and older: apply to affected area not more than 3 to 4 times daily
- children under 2 years of age: consult a doctor

Other information

- store in a cool dry place with lid closed tightly

Inactive ingredients

Aloe barbadensis leaf juice, Arctium lappa root extract, Arnica montana flower extract, blue 1, Boswellia carterii resin extract, Calendula officinalis flower extract, Camellia sinensis leaf extract, camphor, carbomer, Chamomilla recutita (matricaria) flower extract, glycerin, Ilex paraguariensis leaf extract, isopropyl alcohol, isopropyl myristate, Juniperus communis fruit extract, Melissa officinalis extract, silica, tocopheryl acetate, triethanolamine, water, yellow 5

Disclaimer

*This product is not manufactured or distributed by Biofreeze Performance Health, distributor of BioFreeze®Cool the Pain Roll-On Fast Acting Menthol Pain Relief.

Adverse reaction

DISTRIBUTED BY:

RITE AID, 30 HUNTER LANE,

CAMP HILL, PA 17011

www.riteaid.com

PRINCIPAL DISPLAY PANEL

Compare to the active ingredient of Biogreeze®Roll-on*

ROLL-ON

COOLING

PAIN RELIEF

4% MENTHOL

for arthritis, sore muscles, joints & back pain

soothing menthol

diminishing scent

paraben-free

2.5 FL OZ (73 mL)